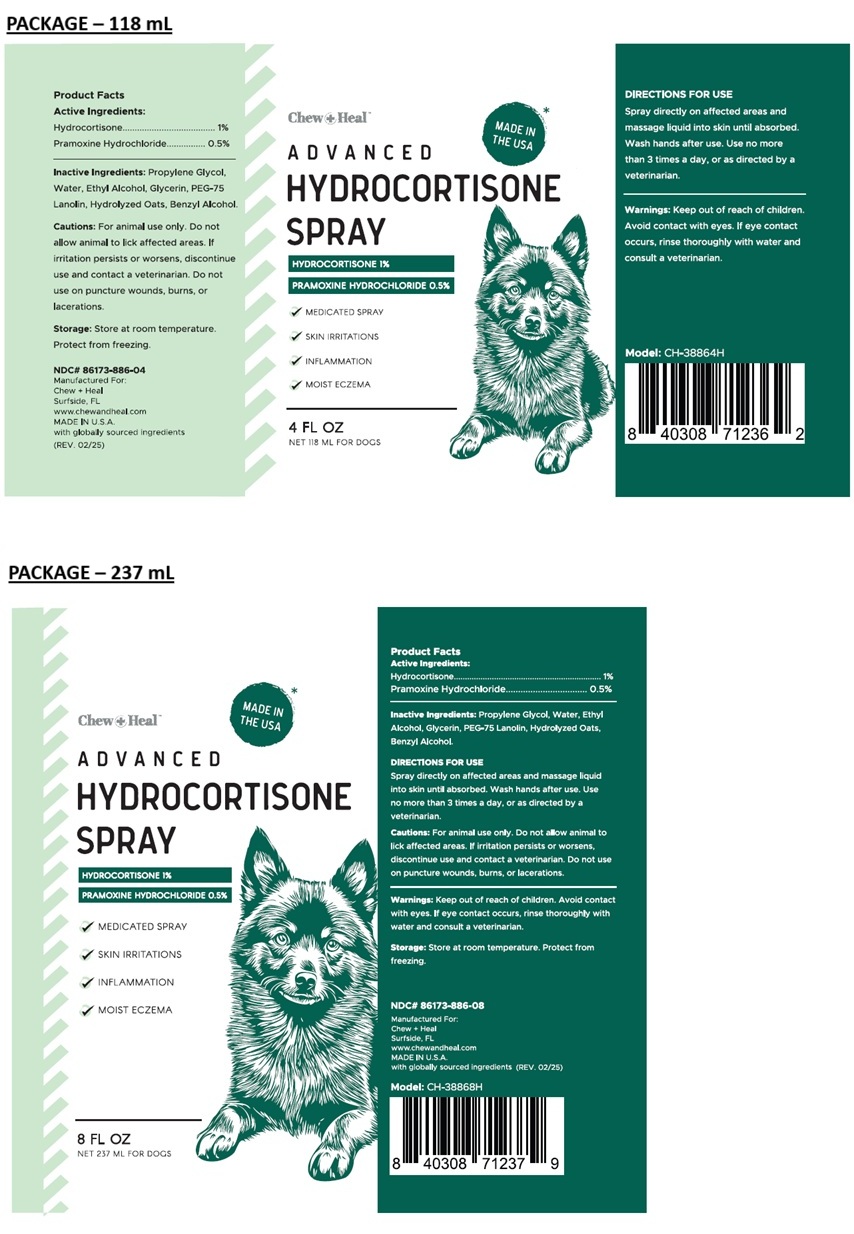 DRUG LABEL: Chew Plus Heal ADVANCED HYDROCORTISONE
NDC: 86173-886 | Form: SPRAY
Manufacturer: Click Industries LLC
Category: animal | Type: OTC ANIMAL DRUG LABEL
Date: 20250311

ACTIVE INGREDIENTS: HYDROCORTISONE 1 g/100 mL; PRAMOXINE HYDROCHLORIDE 0.5 g/100 mL
INACTIVE INGREDIENTS: PROPYLENE GLYCOL; WATER; ALCOHOL; GLYCERIN; PEG-75 LANOLIN; BENZYL ALCOHOL

Chew+Heal™ ADVANCED HYDROCORTISONE SPRAY

Active Ingredients:

Hydrocortisone................................ 1%
Pramoxine Hydrochloride............... 0.5%

Inactive Ingredients:

Propylene Glycol, Water, Ethyl Alcohol, Glycerin, PEG-75 Lanolin, Hydrolyzed Oats, Benzyl Alcohol.

DIRECTIONS FOR USE

Spray directly on affected areas and massage liquid into skin until absorbed. Wash hands after use. Use no more than 3 times a day, or as directed by a veterinarian.

Cautions:

For animal use only. Do not allow animal to lick affected areas. If irritation persists or worsens, discontinue use and contact a veterinarian. Do not use on puncture wounds, burns, or lacerations.

Warnings:

Keep out of reach of children. Avoid contact with eyes. If eye contact occurs, rinse thoroughly with water and consult a veterinarian.

Storage:

Store at room temperature. Protect from freezing.

✓ MEDICATED SPRAY

✓ SKIN IRRITATIONS

✓ INFLAMMATION

✓ MOIST ECZEMA

FOR DOGS

Manufactured For:
Chew + Heal
Surfside, FL
www.chewandheal.com
MADE IN U.S.A.
with globally sourced ingredients